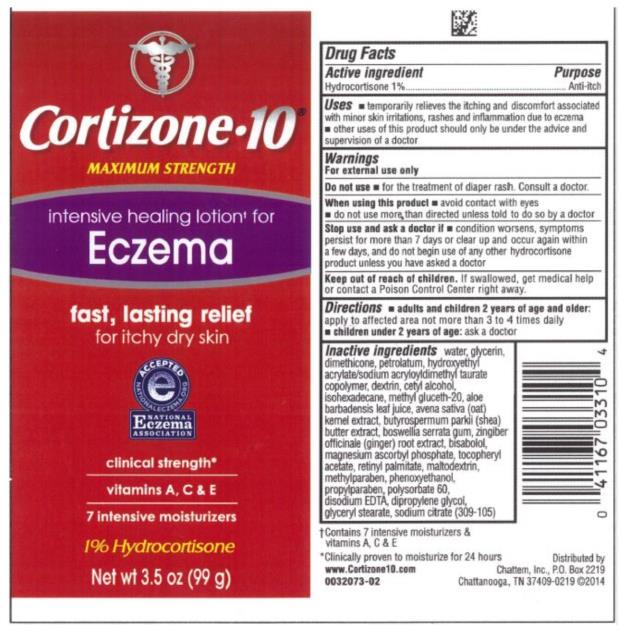 DRUG LABEL: Cortizone 10 Intensive Healing for Eczema
NDC: 41167-0331 | Form: LOTION
Manufacturer: Chattem, Inc.
Category: otc | Type: HUMAN OTC DRUG LABEL
Date: 20231106

ACTIVE INGREDIENTS: HYDROCORTISONE 10 mg/1 g
INACTIVE INGREDIENTS: ALOE VERA LEAF; CETYL ALCOHOL; DIMETHICONE; DIPROPYLENE GLYCOL; EDETATE DISODIUM; GLYCERIN; GLYCERYL MONOSTEARATE; MALTODEXTRIN; METHYLPARABEN; PETROLATUM; PHENOXYETHANOL; POLYSORBATE 60; PROPYLPARABEN; VITAMIN A PALMITATE; SODIUM CITRATE; .ALPHA.-TOCOPHEROL ACETATE, D-; WATER

Cortizone 10 Intensive Healing for Eczema

Active Ingredient:

Hydrocortisone 1%

Purpose

Anti-itch

Uses

- temporarily relieves the itching and discomfort associated with minor skin irritations, rashes, and inflammation, and due to eczema
- other uses of this product should only be under the advice and supervision of a doctor

Warnings

For external use only

Do not use

- for the treatment of diaper rash. Consult a doctor.

When using this product

- avoid contact with eyes
- do not use more than directed unless told to do so by a doctor.

Stop use and ask a doctor if

- condition worsens, symptoms persist for more than 7 days or clear up and occur again within a few days, and do not begin use of any other hydrocortisone product unless you have asked a doctor

Keep out of reach of children.

If swallowed, get medical help or contact a Poison Control Center right away.

Directions

- adults and children 2 years of age and older: apply to affected area not more than 3 to 4 times daily
- children under 2 years of age: ask a doctor

Other information

- contents filled by weight, not volume

Inactive Ingredients

aloe barbadensis leaf juice, avena sativa (oat) kernel extract, bisabolol, boswellia serata gum, butyrospermum parkii (shea) butter extract, cetyl alcohol, dextrin, dimethicone, dipropylene glycol, disodium EDTA, glycerin, glyceryl stearate, hydroxyethyl acrylate/sodium acryloyldimethyl taurate copolymer, isohexadecane, magnesium ascorbyl phosphate, maltodextrin, methyl gluceth-20, methylparaben, petrolatum, phenoxyethanol, polysorbate 60, propylparaben, retinyl palmitate, sodium citrate, tocopheryl acetate, water, singiber officinale (ginger) root extract (283-035)

*Clinically proven to moisturize for 24 hours

**Refers to the ingredient hydrocortisone

†Contains 7 healing moisturizers and vitamins A, C & E

Principal Display Panel

NEW!

Fast, Lasting

Itch Relief

MAXIMUM STRENGTH

Cortizone-10®

INTENSIVE HEALING

LOTION†

ECZEMA

And Itchy, Dry Skin

Dermatologist

Recommended

- 7 intensive moisturizers
- Clinical strength*

With

Restora TM

Botanical &

Vitamin Complex

1% Hydrocortisone Anti-Itch Lotion

DOCTORS

#1 ITCH MEDICINE

RECOMMEND

Net wt 3.5 oz (99 g)